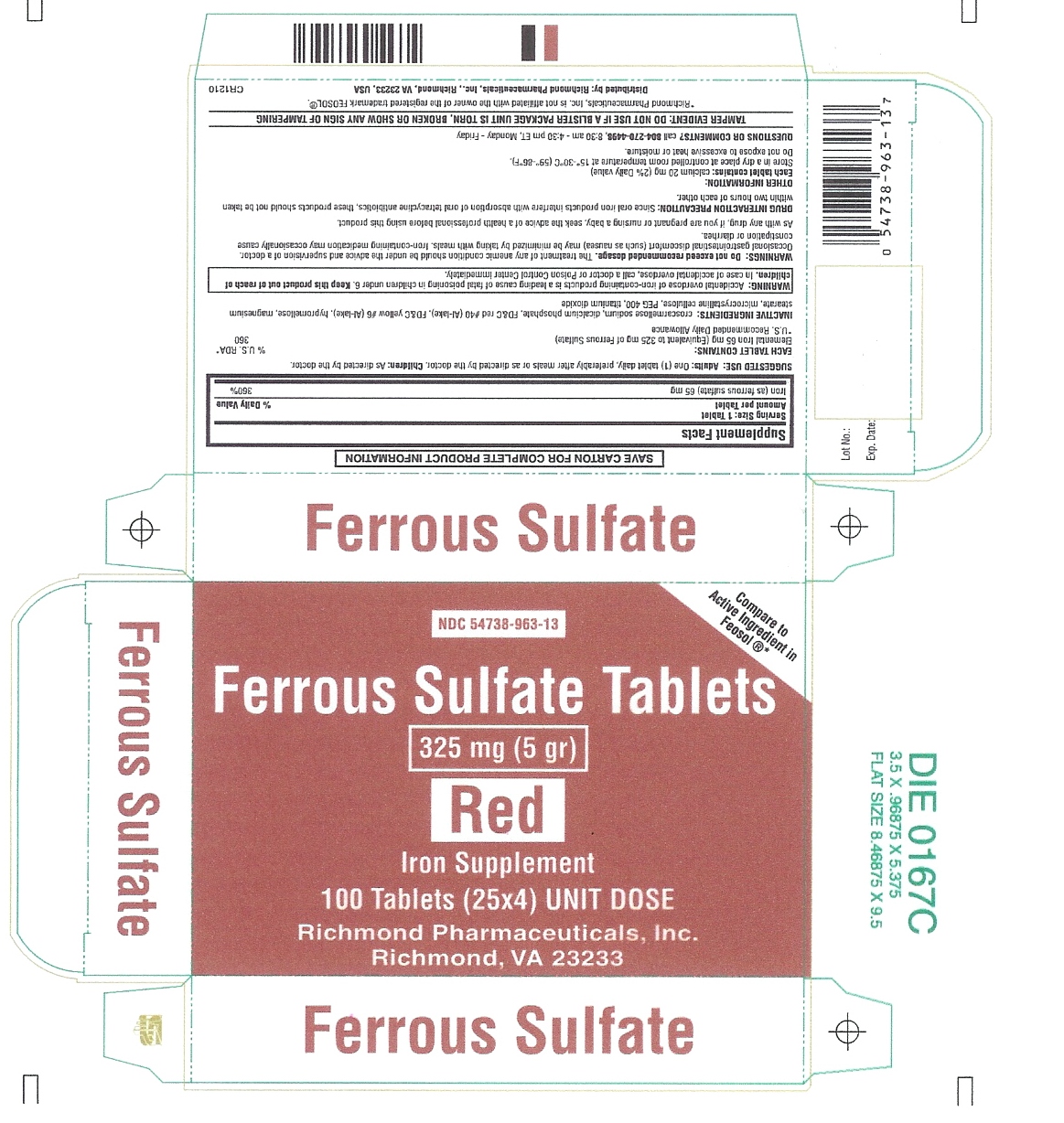 DRUG LABEL: Ferrous Sulfate
NDC: 54738-963 | Form: TABLET
Manufacturer: Richmond Pharmaceuticals Inc.
Category: otc | Type: HUMAN OTC DRUG LABEL
Date: 20241226

ACTIVE INGREDIENTS: FERROUS SULFATE 325 mg/1 1
INACTIVE INGREDIENTS: CROSCARMELLOSE SODIUM; DIBASIC CALCIUM PHOSPHATE DIHYDRATE; FD&C RED NO. 40; FD&C YELLOW NO. 6; HYPROMELLOSES; MAGNESIUM STEARATE; CELLULOSE, MICROCRYSTALLINE; POLYETHYLENE GLYCOL 400; TITANIUM DIOXIDE

Ferrous Sulfate Tablets 325 mg (5 gr)

SAVE CARTON FOR COMPLETE PRODUCT INFORMATION

Supplement Facts
 | % Daily Value
Iron (as ferrous sulfate) 65 mg | 360%

INDICATIONS AND USAGE

SUGGESTED USE:

PURPOSE

Adults:One (1) tablet daily, preferably after meals or as directed by the doctor.

Children:As directed by the doctor.

ACTIVE INGREDIENT

EACH TABLET CONTAINS: % U.S. RDA*

Elemental Iron 65 mg (Equivalent to 325 mg of Ferrous Sulfate) 60

*U.S. Recommended Daily Allowance

INACTIVE INGREDIENTS:

croscarmellose sodium, dicalcium phosphate, FD&C red #40 (Al-lake), FD&C yellow #6 (Al-lake), hypromellose, magnesium stearate, microcrystalline cellulose, PEG 400, titanium dioxide

BOXED WARNING

WARNING: Accidental overdose of iron-containing products is a leading cause of fatal poisoning in children under 6. Keep this product out of reach of children.In case of accidental overdose, call a doctor or Poison Control Center immediately.

WARNINGS:

Do not exceed recommended dosage.The treatment of any anemic condition should be under the advice and supervision of a doctor. Occasional gastrointestinal discomfort (such as nausea) may be minimized by taking with meals. Iron-containing medication may occasionally cause constipation or diarrhea.

As with any drug, if you are pregnant or nursing a baby, seek the advice of a health professional before using this product.

DOSAGE AND ADMINISTRATION

DRUG INTERACTION PRECAUTION:Since oral iron products interfere with absorption of oral tetracycline antibiotics, these products should not be taken within two hours of each other.

OTHER INFORMATION:

Each tablet contains:calcium 20 mg (2% Daily value)

Store in a dry place at controlled room temperature at 15°-30°C (59°-86°F).

Do not expose to excessive heat or moisture.

QUESTIONS OR COMMENTS?

call 804-270-4498, 8:30 am - 4:30 pm ET, Monday – Friday

TAMPER EVIDENT: DO NOT USE IF A BLISTER PACKAGE UNIT IS TORN, BROKEN OR SHOW ANY SIGN OF TAMPERING

*Richmond Pharmaceuticals, Inc. is not affiliated with the owner of the registered trademark FEOSOL®.

Distributed by: Richmond Pharmaceuticals, Inc., Richmond, VA 23233, USA

CR1210

Principle Display Panel

NDC 54738-963-13

Compare to Active Ingredient in Feosol ®*

Ferrous Sulfate Tablets
325 mg (5 gr)

Red

Iron Supplement
100 Tablets (25x4) UNIT DOSE

Richmond Pharmaceuticals, Inc.
Richmond, VA 23233